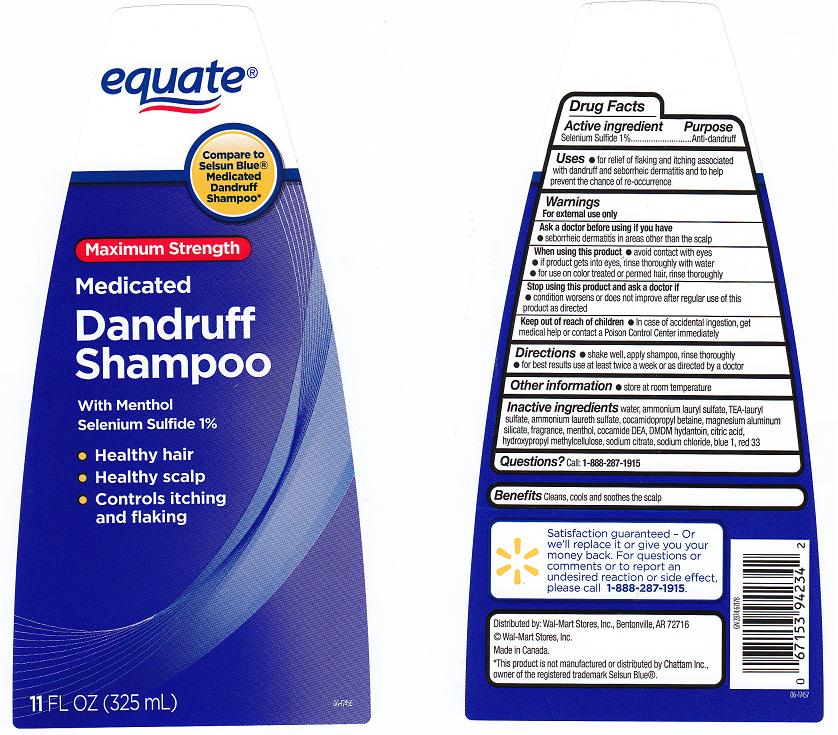 DRUG LABEL: MEDICATED DANDRUFF 
NDC: 49035-610 | Form: SHAMPOO
Manufacturer: WAL-MART STORES INC
Category: otc | Type: HUMAN OTC DRUG LABEL
Date: 20110819

ACTIVE INGREDIENTS: SELENIUM SULFIDE 1.0000 mL/100 mL
INACTIVE INGREDIENTS: WATER; AMMONIUM LAURYL SULFATE; TROLAMINE LAURYL SULFATE; COCAMIDOPROPYL BETAINE; MAGNESIUM ALUMINUM SILICATE; MENTHOL; COCO DIETHANOLAMIDE; DMDM HYDANTOIN; CITRIC ACID MONOHYDRATE; HYPROMELLOSES; FD&C BLUE NO. 1; D&C RED NO. 33; SODIUM CITRATE; SODIUM CHLORIDE; AMMONIUM LAURETH-2 SULFATE

DRUG FACTS

ACTIVE INGREDIENT

SELENIUM SULFIDE 1%

PURPOSE

ANTI-DANDRUFF

USES

FOR RELIEF OF FLAKING AND ITCHING ASSOCIATED WITH DANDRUFF AND SEBORRHEIC DERMATITIS AND TO HELP PREVENT THE CHANCE OF RE-OCCURENCE.

WARNINGS

FOR EXTERNAL USE ONLY.

ASK A DOCTOR BEFORE USING IF YOU HAVE

SEBORRHEIC DERMATITIS IN AREAS OTHER THAN THE SCALP.

WHEN USING THIS PRODUCT

AVOID CONTACT WITH THE EYES.IF CONTACT OCCURS, RINSE EYES THOROUGHLY WITH WATER. FOR USE ON COLOR-TREATED OR PERMED HAIR, RINSE THOROUGHLY.

STOP USING THIS PRODUCT AND ASK A DOCTOR IF

CONDITION WORSENS OR DOES NOT IMPROVE AFTER REGULAR USE OF THIS PRODUCT AS DIRECTED.

KEEP OUT OF REACH OF CHILDREN

IN CASE OF ACCIDENTAL INGESTION, GET MEDICAL HELP OR CONTACT A POISON CONTROL CENTER IMMEDIATELY.

DIRECTIONS

SHAKE WELL, APPLY SHAMPOO, RINSE THOROUGHLY. FOR BEST RESULTS, USE AT LEAST TWICE A WEEK OR AS DIRECTED BY A DOCTOR.

OTHER INFORMATION

STORE AT ROOM TEMPERATURE.

INACTIVE INGREDIENTS

WATER, AMMONIUM LAURYL SULFATE, TEA-LAURYL SULFATE, AMMONIUM LAURETH SULFATE, COCAMIDOPROPYL BETAINE, MAGNESIUM ALUMINUM SILICATE, FRAGRANCE, MENTHOL, COCAMIDE DEA, DMDM HYDANTOIN, CITRIC ACID, HYDROXYPROPYL METHYLCELLULOSE, SODIUM CITRATE, SODIUM CHLORIDE, BLUE 1, RED 33.

QUESTIONS?

CALL: 1-888-287-1915